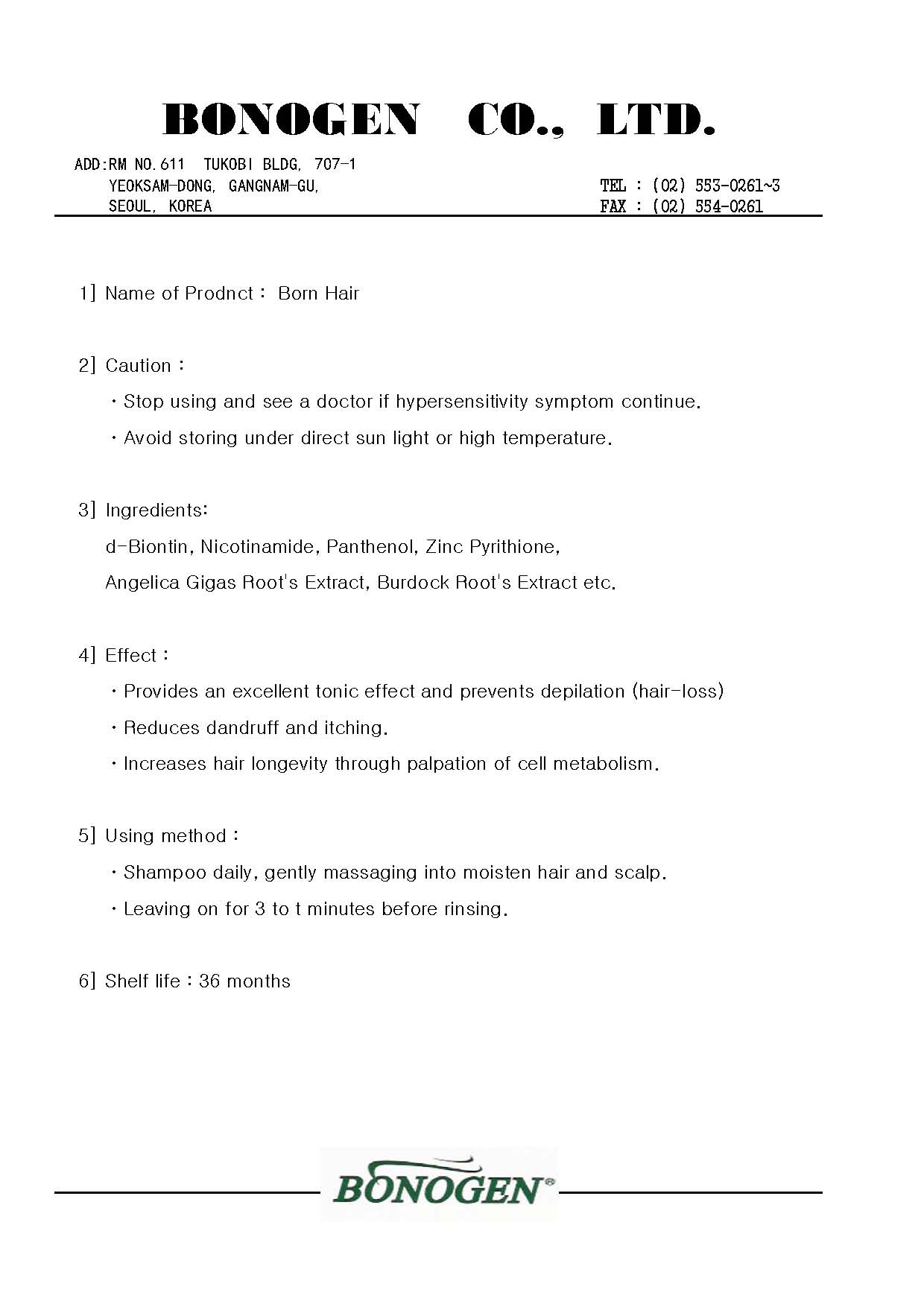 DRUG LABEL: Born Hair
NDC: 50653-4001 | Form: SHAMPOO
Manufacturer: Bonogen Co., Ltd
Category: otc | Type: HUMAN OTC DRUG LABEL
Date: 20110517

ACTIVE INGREDIENTS: PANTHENOL 0.6 g/100 g; BIOTIN 0.06 g/100 g; NADIDE 0.3 g/100 g; PYRITHIONE ZINC 2.1 g/100 g
INACTIVE INGREDIENTS: SODIUM LAURETH SULFATE; COCAMIDOPROPYL BETAINE; EDETATE DISODIUM; JOJOBA OIL; ARCTIUM LAPPA ROOT; WATER

Drug Facts

ACTIVE INGREDIENT

Active ingredients: d-Biotin, Nicontinamide, Panthenol, Zinc Pyrithione

DOSAGE AND ADMINISTRATION

- shampoo daily, gently massaging into moisten hair and scalp
- leaving on for 3 to 5 minutes before rinsing

inactive ingredient: sodium laureth sulfate, cocamidopropyl betaine, edetate disodium, jojoba oil, arctium lappa root, water

PURPOSE

- reduces dandruff and itching
- increases hair longevity through palpation of cell metabolism

- keep out of reach of the children

INDICATIONS AND USAGE

- provides an excellent tonic effect and prevents depilation (hair-loss)

WARNINGS

- stop using and see a doctor if hypersensitivity symptom continues
- avoid storing under direct sun light or high temperature